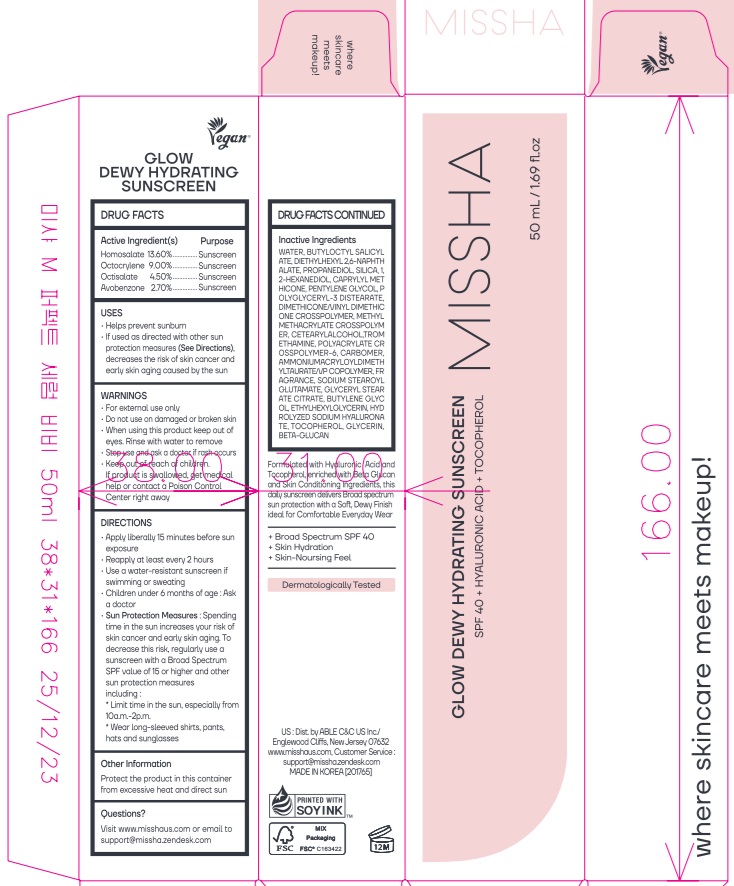 DRUG LABEL: MISSHA GLOW DEWY HDRATING SUNSCREEN
NDC: 13733-248 | Form: CREAM
Manufacturer: Able C&C Co., Ltd.
Category: otc | Type: HUMAN OTC DRUG LABEL
Date: 20260122

ACTIVE INGREDIENTS: AVOBENZONE 2.7 g/100 mL; OCTISALATE 4.5 g/100 mL; HOMOSALATE 13.6 g/100 mL; OCTOCRYLENE 9 g/100 mL
INACTIVE INGREDIENTS: PENTYLENE GLYCOL; CAPRYLYL METHICONE; BUTYLOCTYL SALICYLATE; DIETHYLHEXYL 2,6-NAPHTHALATE; PROPANEDIOL; 1,2-HEXANEDIOL; WATER; SILICON DIOXIDE

MISSHA GLOW DEWY HDRATING SUNSCREEN

Active ingredient(s)
Homosalate 13.60%
Octocrylene 9.00%
Octisalate 4.50%
Avobenzone 2.70%

Purpose

Sunscreen

USES

■ Helps prevent sunburn

■ If used as directed with other sun protection measures (See Directions), decreases the risk of skin cancer and early skin aging caused by the sun

WARNINGS

■ For external use only

■ Do not use on damaged or broken skin

■ When using this product keep out of eyes. Rinse with water to remove

■ Stop use and ask a doctor if rash occurs

■ Keep out of reach of children. If product is swallowed, get medical help

or contact a Poison Control Center right away

Keep out of reach of children.

DIRECTIONS

■ Apply liberally 15 minutes before sun exposure

■ Reapply at least every 2 hours

■ Use a water-resistant sunscreen if swimming or sweating

■ Children under 6months of age: Ask a doctor

■ Sun Protection Measures. Spending time in the sun increases your risk of skin cancer and early skin aging. To decrease this risk, regularly use a sunscreen with SPF value of 15 or higher and other sun protection measures including:

* Limit time in the sun, especially from 10a.m.-2p.m.

* Wear long-sleeved shirts, pants, hats and sunglasses

Other Information

Protect the product in this container from excessive heat and direct sun

Questions?

Visit www.misshaus.com or email to support@missha.zendesk.com

Inactive ingredients

WATER, BUTYLOCTYL SALICYLATE, DIETHYLHEXYL 2,6-NAPHTHALATE, PROPANEDIOL, SILICA, 1,2-HEXANEDIOL, CAPRYLYL METHICONE, PENTYLENE GLYCOL, POLYGLYCERYL-3 DISTEARATE, DIMETHICONE/VINYL DIMETHICONE CROSSPOLYMER, METHYL METHACRYLATE CROSSPOLYMER, CETEARYL ALCOHOL, TROMETHAMINE, POLYACRYLATE CROSSPOLYMER-6, CARBOMER, AMMONIUM ACRYLOYLDIMETHYLTAURATE/VP COPOLYMER, FRAGRANCE, SODIUM STEAROYL GLUTAMATE, GLYCERYL STEARATE CITRATE, BUTYLENE GLYCOL, ETHYLHEXYLGLYCERIN, HYDROLYZED SODIUM HYALURONATE, TOCOPHEROL, GLYCERIN, BETA-GLUCAN